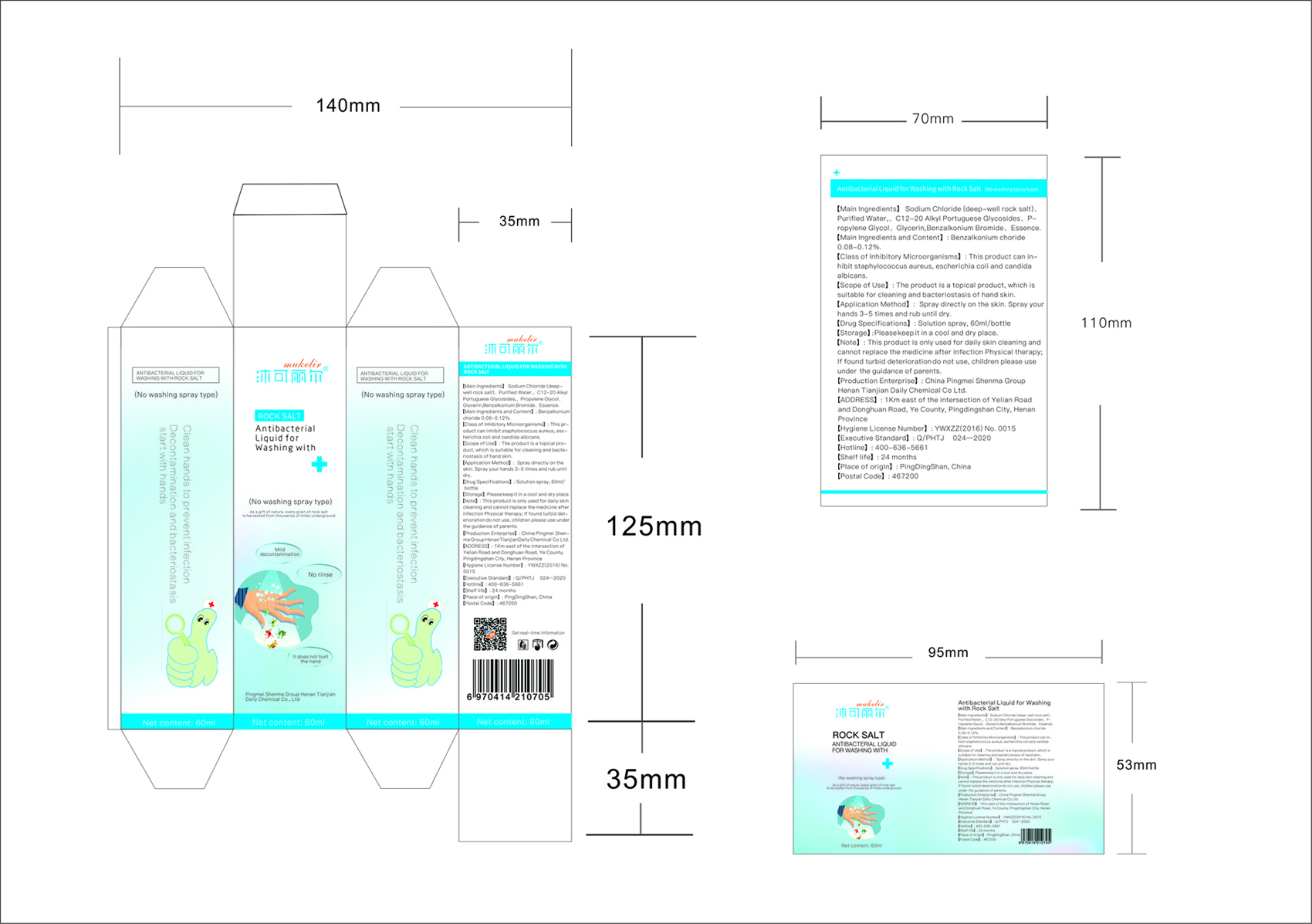 DRUG LABEL: Mukelir Antibacterial Liquid for Washing Hands with Rock Salt
NDC: 76620-001 | Form: SPRAY
Manufacturer: Pingmei Shenma Group Henan Tianjian Daily Chemical Co., Ltd.
Category: otc | Type: HUMAN OTC DRUG LABEL
Date: 20200512

ACTIVE INGREDIENTS: BENZALKONIUM CHLORIDE 0.1 g/100 mL
INACTIVE INGREDIENTS: GLYCERIN; C12-20 ALKYL GLUCOSIDE; SODIUM CHLORIDE; WATER; PROPYLENE GLYCOL

Mukelir Antibacterial Liquid for Washing Hands with Rock Salt

Active Ingredient(s)

0.10% Benzalkonium choride Purpose: Antiseptic

Purpose

Antiseptic, Hand Sanitizer

Use

The product is a topical product, which is suitable for cleaning and bacteriostasis of hand skin.

Warnings

This product is only used for daily skin cleaning and cannot replace the medicine after infection physical therapy

Do not use

If found turbid deterioraion

WHEN USING

Children please use under the guidance of parants

If found turbid deterioration do not use

Keep out of reach of children.

Directions

Spray directly on the skin. Spray your hands 3-5 times and rub until dry.

Other information

Please keep it in a cool and dry place.

Inactive ingredients

Sodium chloride, Purified water, C12-20 Alkyl glucoside, Propylene glycol, glycerin, essence

Package Label - Principal Display Panel

60 mL NDC: 76620-001-01